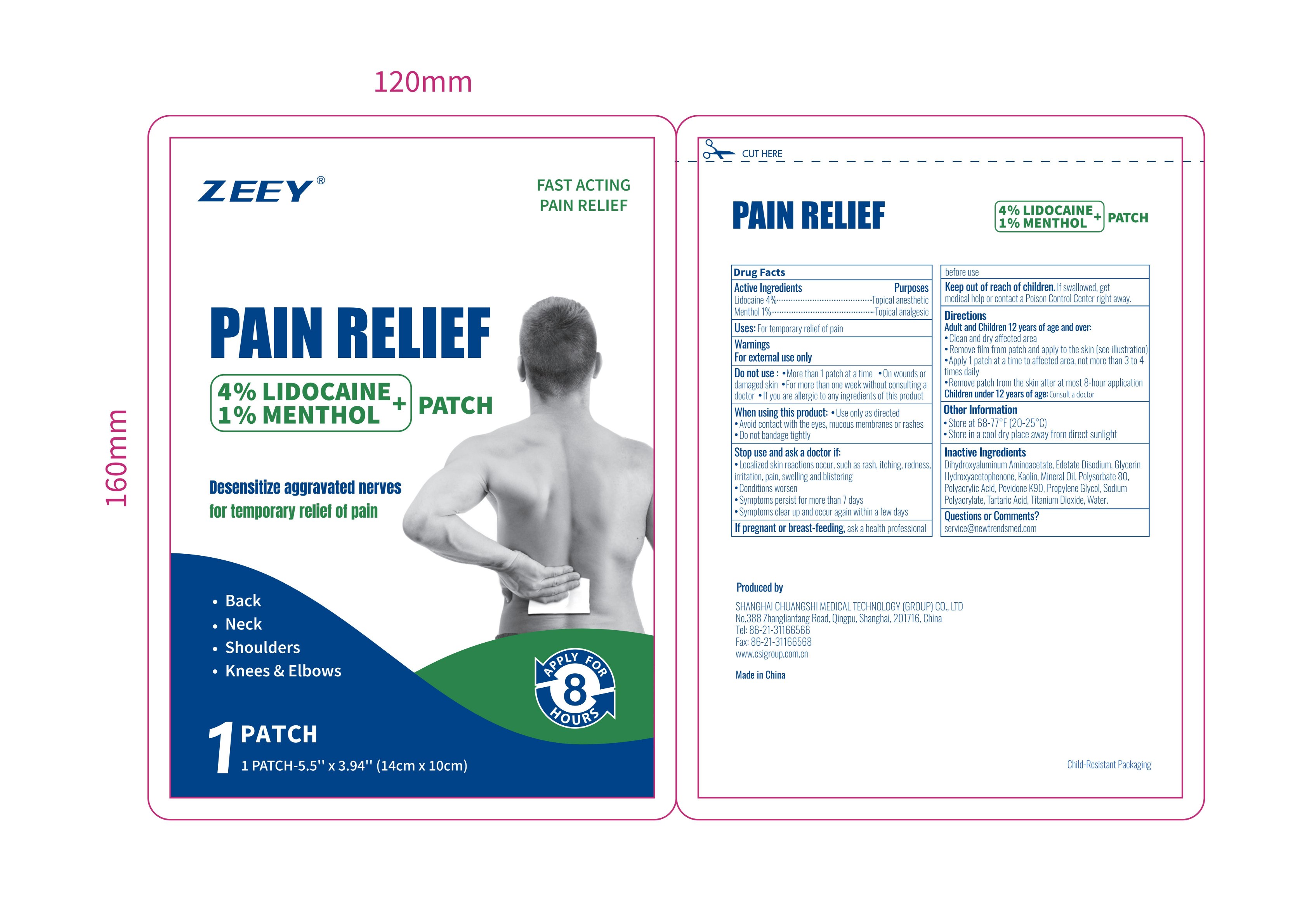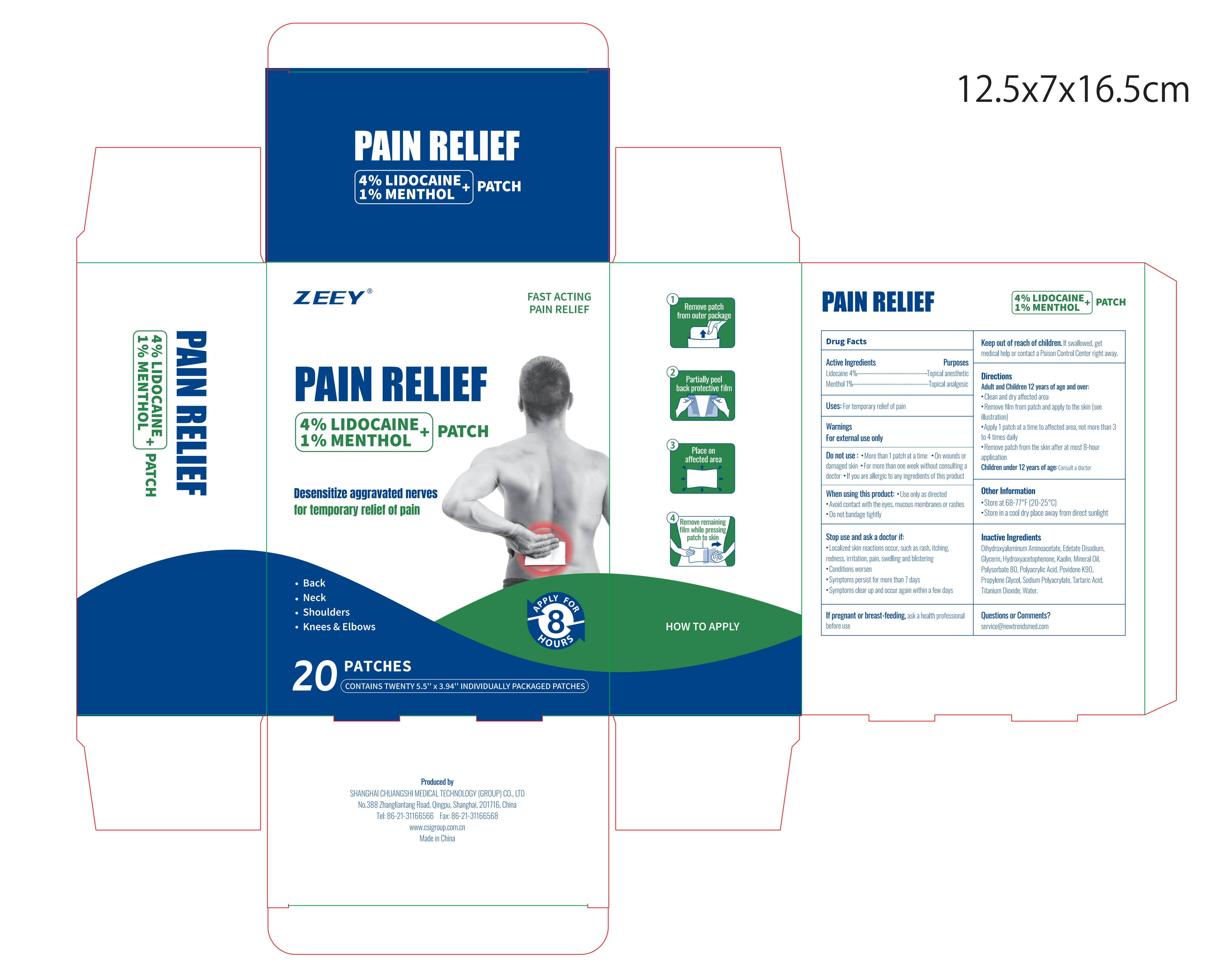 DRUG LABEL: Pain Relief
NDC: 73557-175 | Form: PATCH
Manufacturer: Shanghai Chuangshi Medical Technology (Group) Co., Ltd.
Category: otc | Type: HUMAN OTC DRUG LABEL
Date: 20250922

ACTIVE INGREDIENTS: MENTHOL 0.01 g/1 g; LIDOCAINE 0.04 g/1 g
INACTIVE INGREDIENTS: KAOLIN; TARTARIC ACID; WATER; DIHYDROXYALUMINUM AMINOACETATE ANHYDROUS; PROPYLENE GLYCOL; POLYACRYLIC ACID (250000 MW); SODIUM POLYACRYLATE (2500000 MW); TITANIUM DIOXIDE; MINERAL OIL; POLYSORBATE 80; GLYCERIN; EDETATE DISODIUM; POVIDONE K90; HYDROXYACETOPHENONE

73557-175

Active Ingredient

Lidocaine 4% w/w ...... Purpose: Topical anesthetic

Menthol 1% w/w ...... Purpose: Topical analgesic

Purposes

Topical anesthetic (Lidocaine)

Topical analgesic (Menthol)

Uses

For temporary relief of pain

Warnings

For external use only

When using this product:

- Use only as directed
- Avoid contact with the eyes, mucous membranes or rashes
- Do not bandage tightly

Do not use:

- More than 1 patch at a time
- On wounds or damaged skin
- For more than one week without consulting a doctor
- If you are allergic to any ingredients of this product

Stop use and ask a doctor if:

- Localized skin reactions occur, such as rash, itching, redness, irritation, pain, swelling and blistering
- Condition worsen
- Symptoms persist for more than 7 days
- Symptoms clear up and occur again within a few days

If pregnant or breast-feeding,

Ask a health professional before use

Keep out of reach of children.

If swallowed, get medical help or contact a Poison Control Center right away

Directions

Adult and Children 12 years of age and over:

- Clean and dry affected area
- Remove ﬁlm from patch and apply to the skin (see illustration)
- Apply 1 patch at a time to affected area, not more than 3 to 4 times daily
- Remove patch from the skin after at most 8-hour application

Children under 12 years of age:Consult a doctor

Inactive Ingredients

Dihydroxyaluminium Aminoacetate, Edetate Disodium,Glycerin, Hydroxyacetophenone,Kaolin, Mineral Oil,Polysorbate 80, Polyacrylic Acid, Povidone K90, Propylene Glycol,Sodium Polyacrylate,Tartaric Acid,Titanium Dioxide,Water

Questions or Comments

service@newtrendsmed.com

Other information

- Store at 68-77℉ (20-25℃)
- Store in a cool dry place away from direct sunlight